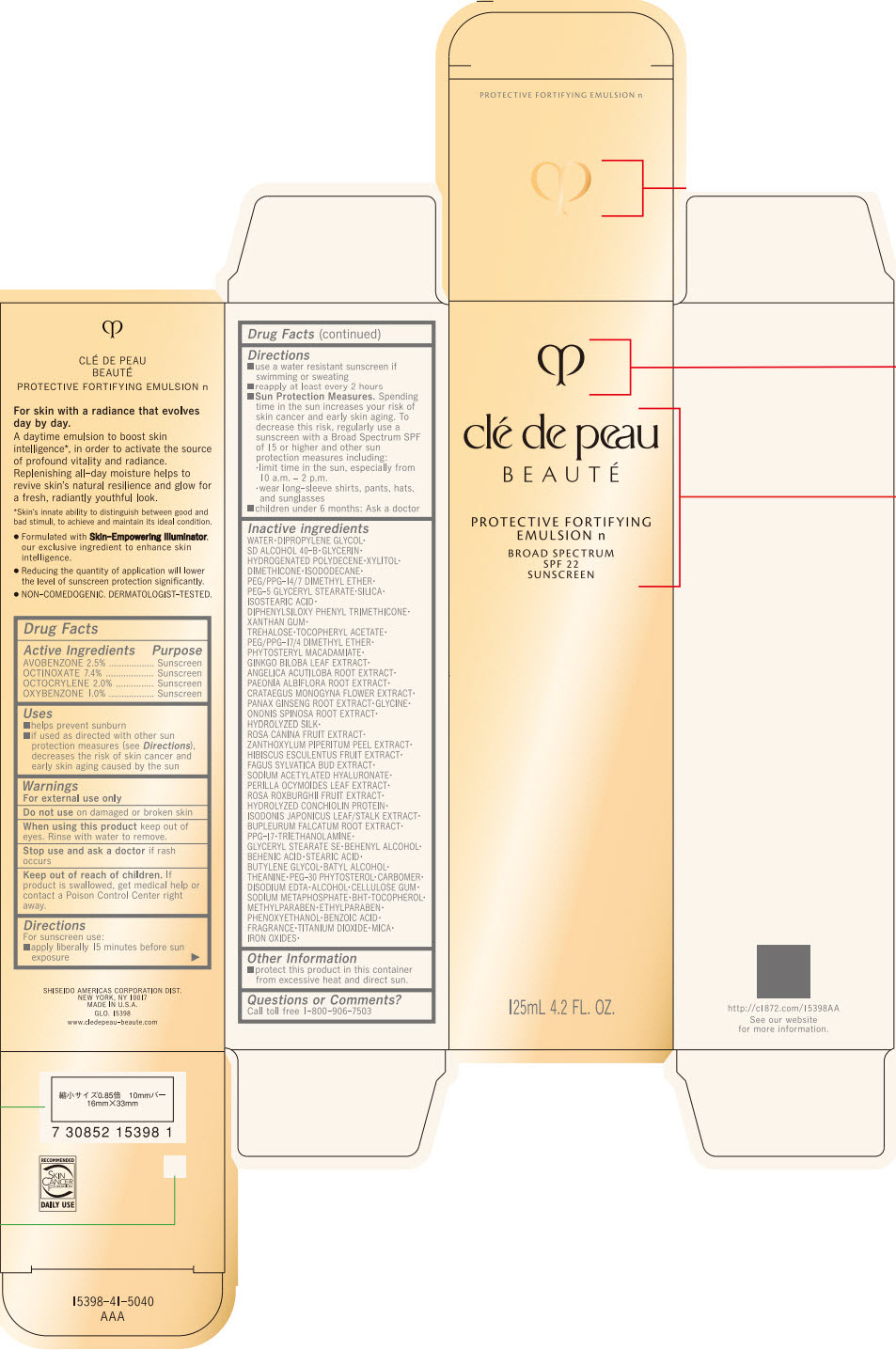 DRUG LABEL: CLE DE PEAU BEAUTE PROTECTIVE FORTIFYING n
NDC: 58411-454 | Form: EMULSION
Manufacturer: SHISEIDO AMERICAS CORPORATION
Category: otc | Type: HUMAN OTC DRUG LABEL
Date: 20260105

ACTIVE INGREDIENTS: AVOBENZONE 3200 mg/125 mL; OCTINOXATE 9472 mg/125 mL; OCTOCRYLENE 2560 mg/125 mL; OXYBENZONE 1280 mg/125 mL
INACTIVE INGREDIENTS: PEG/PPG-17/4 DIMETHYL ETHER; PHYTOSTERYL MACADAMIATE; GINKGO; ANGELICA ACUTILOBA ROOT; PAEONIA LACTIFLORA ROOT; CRATAEGUS MONOGYNA FLOWER; ASIAN GINSENG; GLYCINE; ONONIS SPINOSA ROOT; SODIUM ACETYLATED HYALURONATE; WATER; DIPROPYLENE GLYCOL; GLYCERIN; HYDROGENATED POLYDECENE TYPE I; XYLITOL; DIMETHICONE; ISODODECANE; PEG/PPG-14/7 DIMETHYL ETHER; PEG-5 GLYCERYL STEARATE; SILICON DIOXIDE; ISOSTEARIC ACID; DIPHENYLSILOXY PHENYL TRIMETHICONE; XANTHAN GUM; TREHALOSE; .ALPHA.-TOCOPHEROL ACETATE, DL-; ROSA ROXBURGHII FRUIT; BUPLEURUM FALCATUM ROOT; PPG-17; TROLAMINE; GLYCERYL MONOSTEARATE; DOCOSANOL; BEHENIC ACID; STEARIC ACID; BUTYLENE GLYCOL; BATILOL; THEANINE; CARBOMER HOMOPOLYMER, UNSPECIFIED TYPE; EDETATE DISODIUM; ALCOHOL; CARBOXYMETHYLCELLULOSE SODIUM, UNSPECIFIED; SODIUM POLYMETAPHOSPHATE; BUTYLATED HYDROXYTOLUENE; .ALPHA.-TOCOPHEROL; METHYLPARABEN; ETHYLPARABEN; PHENOXYETHANOL; BENZOIC ACID; TITANIUM DIOXIDE; MICA; FERRIC OXIDE RED; FERRIC OXIDE YELLOW; FERROSOFERRIC OXIDE

CLÉ DE PEAU BEAUTÉ PROTECTIVE FORTIFYING EMULSION n

Drug Facts

ACTIVE INGREDIENT

Active ingredients | Purpose
AVOBENZONE 2.5% | Sunscreen
OCTINOXATE 7.4% | Sunscreen
OCTOCRYLENE 2.0% | Sunscreen
OXYBENZONE 1.0% | Sunscreen

Uses

- helps prevent sunburn
- if used as directed with other sun protection measures (see Directions), decreases the risk of skin cancer and early skin aging caused by the sun

Warnings

For external use only

Do not useon damaged or broken skin

WHEN USING

When using this productkeep out of eyes. Rinse with water to remove.

Stop use and ask a doctorif rash occurs

Keep out of reach of children.If product is swallowed, get medical help or contact a Poison Control Center right away.

Directions

For sunscreen use:

- apply liberally 15 minutes before sun exposure
- use a water resistant sunscreen if swimming or sweating
- reapply at least every 2 hours
- Sun Protection Measures. Spending time in the sun increases your risk of skin cancer and early skin aging. To decrease this risk, regularly use a sunscreen with a broad spectrum SPF of 15 or higher and other sun protection measures including:
  - limit time in the sun, especially from 10 a.m. – 2 p.m.
  - wear long-sleeve shirts, pants, hats, and sunglasses
- children under 6 months: Ask a doctor

Inactive Ingredients

WATER ∙ DIPROPYLENE GLYCOL ∙ SD ALCOHOL 40-B ∙ GLYCERIN ∙ HYDROGENATED POLYDECENE ∙ XYLITOL・DIMETHICONE ∙ ISODODECANE ∙ PEG/PPG-14/7 DIMETHYL ETHER ∙ PEG-5 GLYCERYL STEARATE ∙ SILICA ∙ ISOSTEARIC ACID ∙ DIPHENYLSILOXY PHENYL TRIMETHICONE ∙ XANTHAN GUM ∙ TREHALOSE ∙ TOCOPHERYL ACETATE ∙ PEG/PPG ∙ 17/4 DIMETHYL ETHER ∙ PHYTOSTERYL MACADAMIATE ∙ GINKGO BILOBA LEAF EXTRACT ∙ ANGELICA ACUTILOBA ROOT EXTRACT ∙ PAEONIA ALBIFLORA ROOT EXTRACT ∙ CRATAEGUS MONOGYNA FLOWER EXTRACT ∙ PANAX GINSENG ROOT EXTRACT ∙ GLYCINE ∙ ONONIS SPINOSA ROOT EXTRACT ∙ HYDROLYZED SILK ∙ ROSA CANINA FRUIT EXTRACT ∙ ZANTHOXYLUM PIPERITUM PEEL EXTRACT ∙ HIBISCUS ESCULENTUS FRUIT EXTRACT ∙ FAGUS SYLVATICA BUD EXTRACT ∙ SODIUM ACETYLATED HYALURONATE ∙ PERILLA OCYMOIDES LEAF EXTRACT ∙ ROSA ROXBURGHII FRUIT EXTRACT ∙ HYDROLYZED CONCHIOLIN PROTEIN ∙ ISODONIS JAPONICUS LEAF/STALK EXTRACT ∙ BUPLEURUM FALCATUM ROOT EXTRACT ∙ PPG-17 ∙ TRIETHANOLAMINE ∙ GLYCERYL STEARATE SE ∙ BEHENYL ALCOHOL ∙ BEHENIC ACID ∙ STEARIC ACID ∙ BUTYLENE GLYCOL ∙ BATYL ALCOHOL ∙ THEANINE ∙ PEG-30 PHYTOSTEROL ∙ CARBOMER ∙ DISODIUM EDTA・ALCOHOL ∙ CELLULOSE GUM ∙ SODIUM METAPHOSPHATE ∙ BHT ∙ TOCOPHEROL ∙ METHYLPARABEN ∙ ETHYLPARABEN ∙ PHENOXYETHANOL ∙ BENZOIC ACID ∙ FRAGRANCE ∙ TITANIUM DIOXIDE ∙ MICA ∙ IRON OXIDES ∙

Other information

- protect this product in this container from excessive heat and direct sun.

Questions or comments?

Call toll free 1-800-906-7503

PRINCIPAL DISPLAY PANEL - 125 mL Container Carton

clé de peau
BEAUTÉ

PROTECTIVE FORTIFYING
EMULSON n

BROAD SPECTRUM
SPF 22
SUNSCREEN

125mL 4.2 FL. OZ.